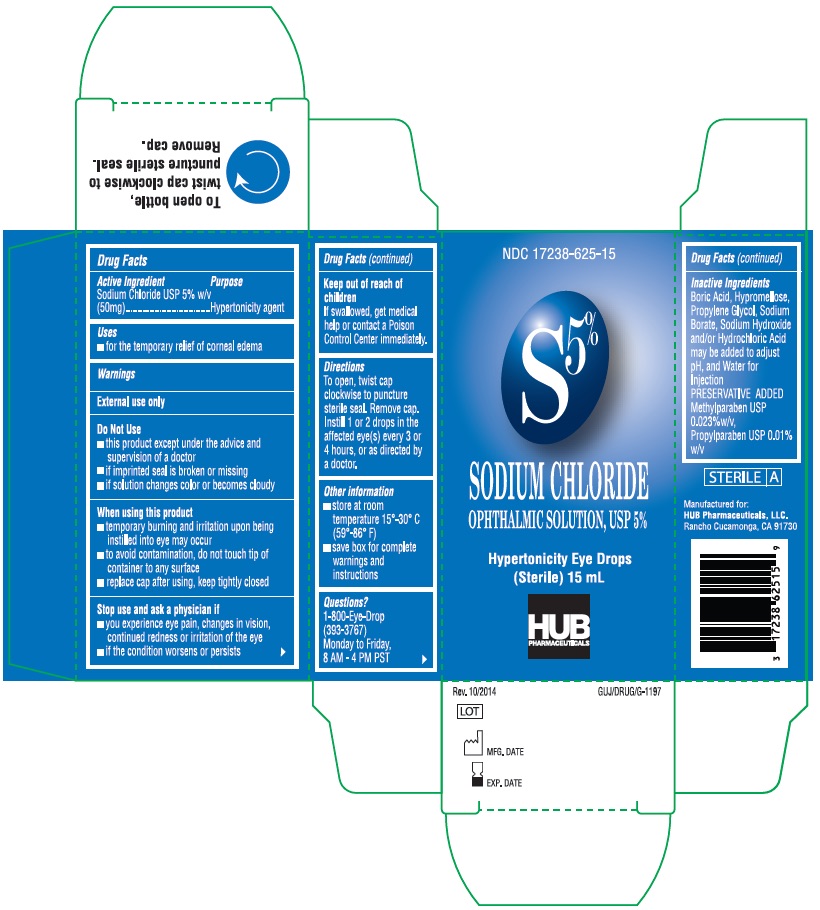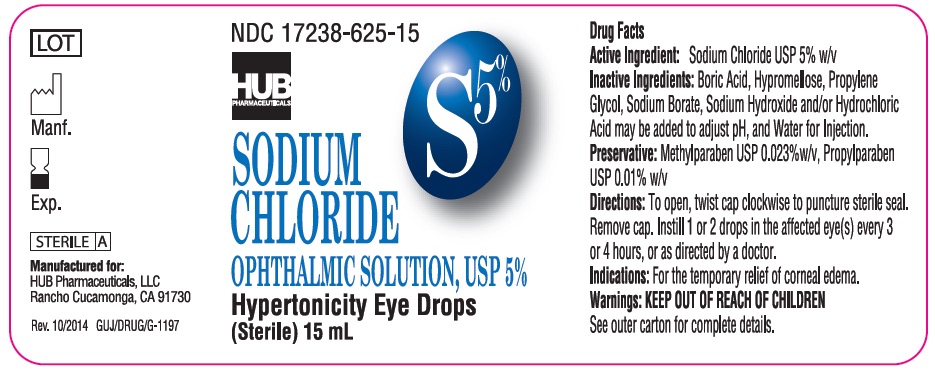 DRUG LABEL: Sodium Chloride
NDC: 17238-625 | Form: SOLUTION/ DROPS
Manufacturer: HUB Pharmaceuticals
Category: otc | Type: HUMAN OTC DRUG LABEL
Date: 20171213

ACTIVE INGREDIENTS: SODIUM CHLORIDE 50 mg/1 mL
INACTIVE INGREDIENTS: METHYLPARABEN; PROPYLPARABEN; BORIC ACID; HYPROMELLOSES; PROPYLENE GLYCOL; SODIUM BORATE; WATER; SODIUM HYDROXIDE; HYDROCHLORIC ACID

Sodium Chloride 5% Solution USP (Sterile)

Drug Facts:

Active Ingredient; (each mL contains) | Purpose
Sodium Chloride USP; 5% w/v (50mg) | Hypertonicity agent

Inactive Ingredients:

Boric Acid, Hypromellose, Propylene Glycol, Sodium Hydroxide and/or Hydrochloric Acid may be added to adjust pH, and Water for Injection.

Preservative:

Methylparaben | USP 0.023% w/v
Propylparaben | USP 0.01% w/v

Directions:

- To open, twist cap clockwise to puncture sterile seal.
- Remove cap.
- Instill 1 or 2 drops in the affected eye(s) every 3 or 4 hours as needed or directed by a doctor.

Dosage & Administration:

Instill 1 or 2 drops in the affected eye(s) every 3 or 4 hours as needed or directed by a doctor.

Indications:

For the temporaty relief of corneal edema.

PURPOSE

For the temporaty relief of corneal edema.

WARNINGS

External use only

Do Not Use

- this product except under the advice and supervision of a doctor
- if imprinted seal is broken or missing
- if solution changes color or becomes cloudy

When using this product:

- temporoary burning and iritation upon being instilled into eye may occur
- To avoid contamination, do not touch top of container to any surface
- Replace cap after using, keep tightly closed

In case of accidental ingestion, seek professional help or contact a Poision Control Center immediately.

Stop use and ask a doctor if:

- you experience eye pain, changes in vision, continued redness, or irritation of the eye.
- if the condition worses or persists

save box for complete warnings and instructions

Keep out of reach of children

If swallowed, get medical help for contact a Poison Control Center immediately.

STORAGE AND HANDLING

Store at room temperature 15°-30°C (59°-86°F).

Questions?

1-800-Eye-Drop (393-3767)

Monday to Friday 8 AM - 4 PM PST

REPRESENTATIVE PACKAGING:

Sodium Chloride Solution Label

Sodium Chloride Solution Box